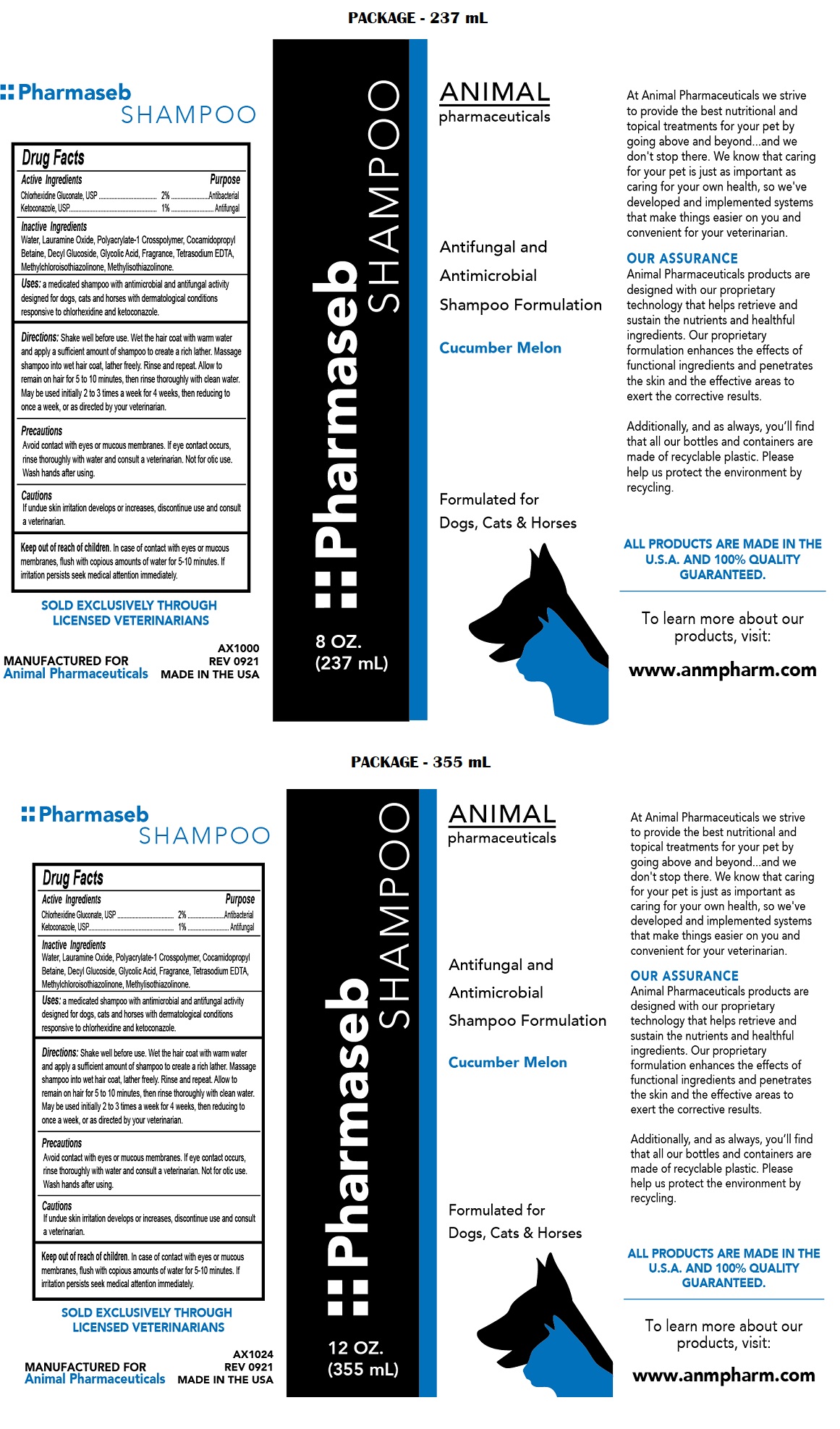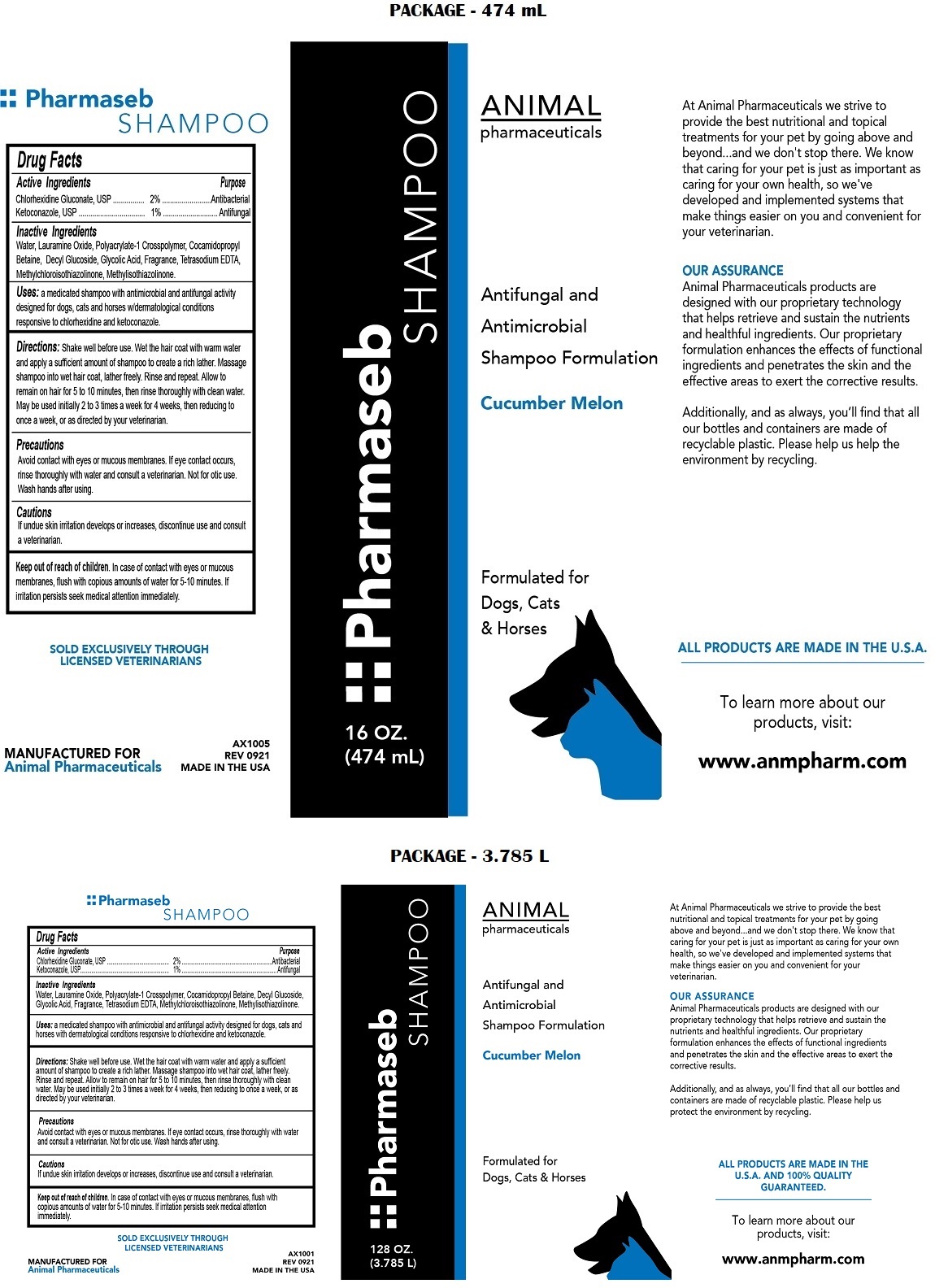 DRUG LABEL: Pharmaseb
NDC: 68898-117 | Form: SHAMPOO
Manufacturer: Animal Pharmaceuticals
Category: animal | Type: OTC ANIMAL DRUG LABEL
Date: 20221121

ACTIVE INGREDIENTS: CHLORHEXIDINE GLUCONATE 2 g/100 mL; KETOCONAZOLE 1 g/100 mL
INACTIVE INGREDIENTS: WATER; LAURAMINE OXIDE; COCAMIDOPROPYL BETAINE; DECYL GLUCOSIDE; GLYCOLIC ACID; EDETATE SODIUM; METHYLCHLOROISOTHIAZOLINONE; METHYLISOTHIAZOLINONE

Pharmaseb SHAMPOO

Active Ingredients

Chlorhexidine Gluconate, USP 2%
Ketoconazole, USP 1%

Purpose

Antibacterial
Antifungal

Inactive Ingredients

Water, Lauramine Oxide, Polyacrylate-1 Crosspolymer, Cocamidopropyl Betaine, Decyl Glucoside, Glycolic Acid, Fragrance, Tetrasodium EDTA, Methylchloroisothiazolinone, Methylisothiazolinone.

Uses:

a medicated shampoo with antimicrobial and antifungal activity designed for dogs, cats and horses with dermatological conditions responsive to chlorhexidine and ketoconazole.

Directions:

Shake well before use. Wet the hair coat with warm water and apply a sufficient amount of shampoo to create a richer lather. Massage shampoo into wet hair coat, lather freely. Rinse and repeat. Allow to remain on hair for 5 to 10 minutes, then rinse thoroughly with clean water. May be used initially 2 to 3 times a week for 4 weeks, then reducing to once a week, or as directed by your veterinarian.

Precautions

Avoid contact with eyes or mucous membranes. If eye contact occurs, rinse thoroughly with water and consult a veterinarian. Not for otic use. Wash hands after using.

Cautions

If undue skin irritation develops or increases, discontinue use and consult a veterinarian.

Keep out of reach of children. In case of contact with eyes or mucous membranes, flush with copious amounts of water for 5-10 minutes. If irritation persists seek medical attention immediately.

Antifungal and Antimicrobial Shampoo Formulation

Cucumber Melon

Formulated for Dogs, Cats & Horses

At Animal Pharmaceuticals we strive to provide the best nutritional and topical treatments for your pet by going above and beyond.... and we don't stop there. We know that caring for your pet is just as important as caring for your own health, so we've developed and implemented systems that make things easier on you and convenient for your veterinarian.

OUR ASSURANCE

Animal Pharmaceuticals products are designed with our proprietary technology that helps retrieve and sustain the nutrients and healthful ingredients. Our proprietary formulation enhances the effects of functional ingredients and penetrates the skin and the effective areas to exert the corrective results.

Additionally, and as always, you'll find that all our bottles and containers are made of recyclable plastic. Please help us protect the environment by recycling.

ALL PRODUCTS ARE MADE IN THE U.S.A. AND 100% QUALITY GUARANTEED.

To learn more about our products, visit:

www.anmpharm.com

SOLD EXCLUSIVELY THROUGH LICENSED VETERINARIANS

MANUFACTURED FOR
Animal Pharmaceuticals

MADE IN THE USA